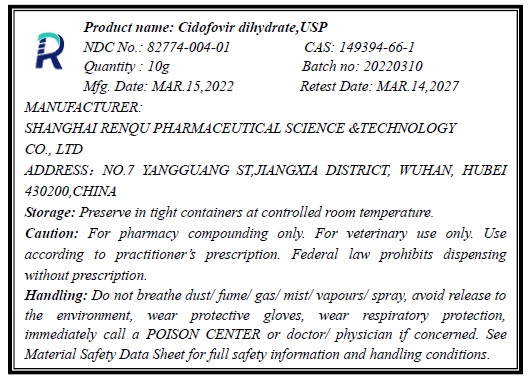 DRUG LABEL: Cidofovir Dihydrate
NDC: 82774-004 | Form: POWDER
Manufacturer: Shanghai Renqu Pharmaceutical Science & Technology Co., Ltd.
Category: other | Type: BULK INGREDIENT - ANIMAL DRUG
Date: 20220722

ACTIVE INGREDIENTS: CIDOFOVIR 1 g/1 g

Cidofovir Dihydrate